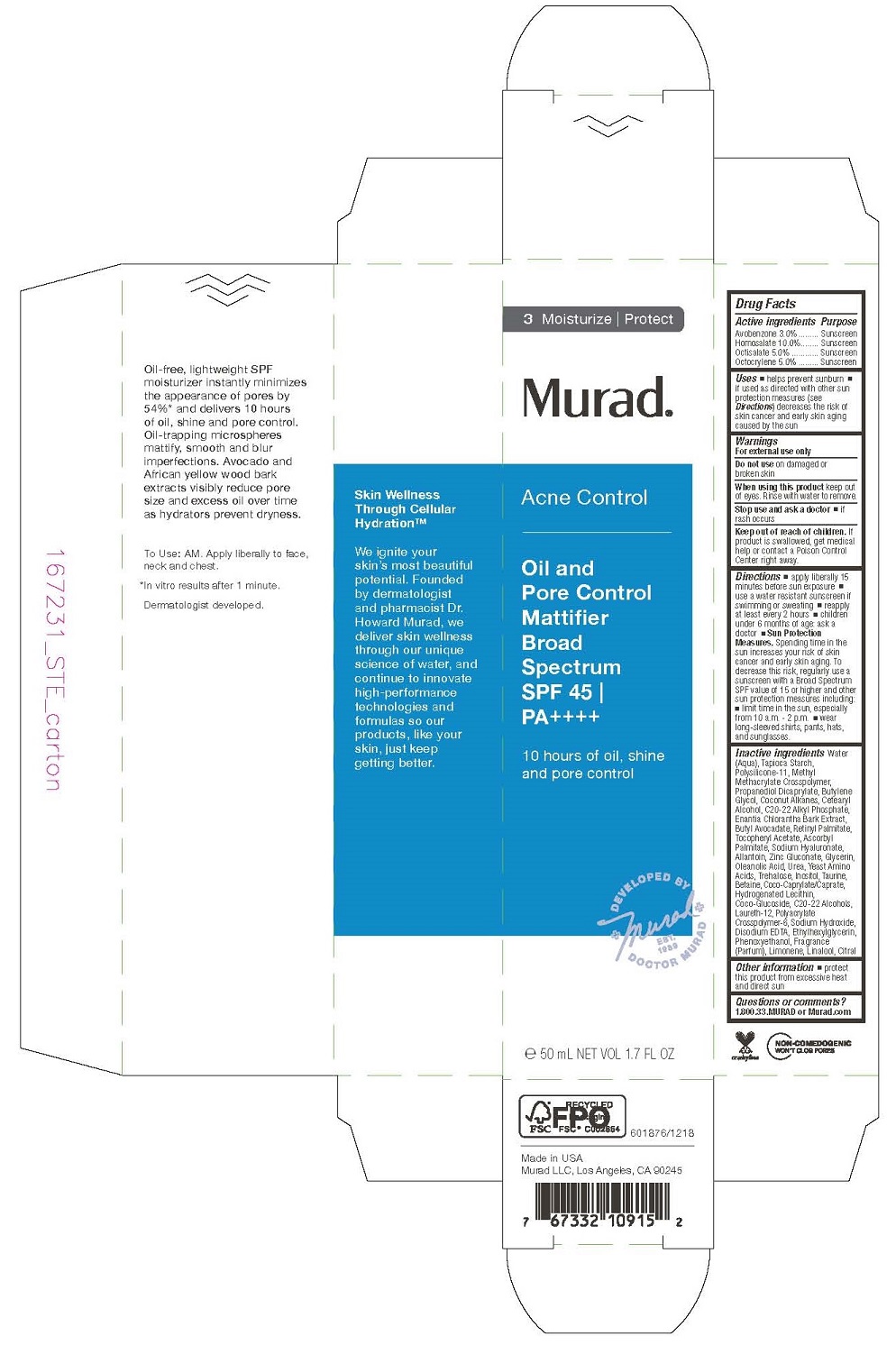 DRUG LABEL: MURAD - ACNE CONTROL - oil AND PORE CONTROL MATTIFIER 
NDC: 70381-101 | Form: LOTION
Manufacturer: Murad, LLC
Category: otc | Type: HUMAN OTC DRUG LABEL
Date: 20200415

ACTIVE INGREDIENTS: AVOBENZONE 3 g/100 mL; HOMOSALATE 10 g/100 mL; OCTISALATE 5 g/100 mL; OCTOCRYLENE 5 g/100 mL
INACTIVE INGREDIENTS: WATER; STARCH, TAPIOCA; DIMETHICONE/VINYL DIMETHICONE CROSSPOLYMER (SOFT PARTICLE); METHYL METHACRYLATE/GLYCOL DIMETHACRYLATE CROSSPOLYMER; PROPANEDIOL DICAPRYLATE; BUTYLENE GLYCOL; COCONUT ALKANES; CETOSTEARYL ALCOHOL; C20-22 ALKYL PHOSPHATE; ANNICKIA CHLORANTHA BARK; BUTYL AVOCADATE; VITAMIN A PALMITATE; .ALPHA.-TOCOPHEROL ACETATE; ASCORBYL PALMITATE; HYALURONATE SODIUM; ALLANTOIN; ZINC GLUCONATE; GLYCERIN; OLEANOLIC ACID; UREA; AMINO ACIDS, SOURCE UNSPECIFIED; TREHALOSE; INOSITOL; TAURINE; BETAINE; COCOYL CAPRYLOCAPRATE; HYDROGENATED SOYBEAN LECITHIN; COCO GLUCOSIDE; C20-22 ALCOHOLS; LAURETH-12; AMMONIUM ACRYLOYLDIMETHYLTAURATE, DIMETHYLACRYLAMIDE, LAURYL METHACRYLATE AND LAURETH-4 METHACRYLATE COPOLYMER, TRIMETHYLOLPROPANE TRIACRYLATE CROSSLINKED (45000 MPA.S); SODIUM HYDROXIDE; EDETATE DISODIUM; ETHYLHEXYLGLYCERIN; PHENOXYETHANOL; LIMONENE, (+)-; LINALOOL, (+)-; CITRAL

MURAD - ACNE CONTROL - OIL AND PORE CONTROL MATTIFIER SPF-45

ACTIVE INGREDIENTS

Avobenzone 3.0%
Homosalate 10.0%
Octisalate 5.0%
Octocrylene 5.0%

PURPOSE

SUNSCREEN

USES

■ helps prevent sunburn

■ if used as directed with other sun protection measures (see Directions) decreases the risk of skin cancer and early skin aging caused by the sun

WARNINGS

For external use only
Do not use on damaged or broken skin
When using this product keep out of eyes. Rinse with water to remove.
Stop use and ask a doctor ■ if rash occurs

Keep out of reach of children. If product is swallowed, get medical help or contact a Poison Control Center right away.

DIRECTIONS

Directions ■ apply liberally 15 minutes before sun exposure ■ use a water resistant sunscreen if swimming or sweating ■ reapply at least every 2 hours ■ children under 6 months of age: ask a doctor ■ Sun Protection Measures. Spending time in the sun increases your risk of skin cancer and early skin aging. To decrease this risk, regularly use a sunscreen with a Broad Spectrum SPF value of 15 or higher and other sun protection measures including: ■ limit time in the sun, especially from 10 a.m. - 2 p.m. ■ wear long-sleeved shirts, pants, hats, and sunglasses.

INACTIVE INGREDIENTS

Water (Aqua), Tapioca Starch, Polysilicone-11, Methyl Methacrylate Crosspolymer, Propanediol Dicaprylate, Butylene Glycol, Coconut Alkanes, Cetearyl Alcohol, C20-22 Alkyl Phosphate, Enantia Chlorantha Bark Extract, Butyl Avocadate, Retinyl Palmitate, Tocopheryl Acetate, Ascorbyl Palmitate, Sodium Hyaluronate, Allantoin, Zinc Gluconate, Glycerin, Oleanolic Acid, Urea, Yeast Amino Acids, Trehalose, Inositol, Taurine, Betaine, Coco-Caprylate/Caprate, Hydrogenated Lecithin, Coco-Glucoside, C20-22 Alcohols, Laureth-12, Polyacrylate Crosspolymer-6, Sodium Hydroxide, Disodium EDTA, Ethylhexylglycerin,
Phenoxyethanol, Fragrance (Parfum), Limonene, Linalool, Citral

OTHER INFORMATION

■ protect this product from excessive heat and direct sun

QUESTIONS OR COMMENTS?

1.800.33.MURAD or Murad.com